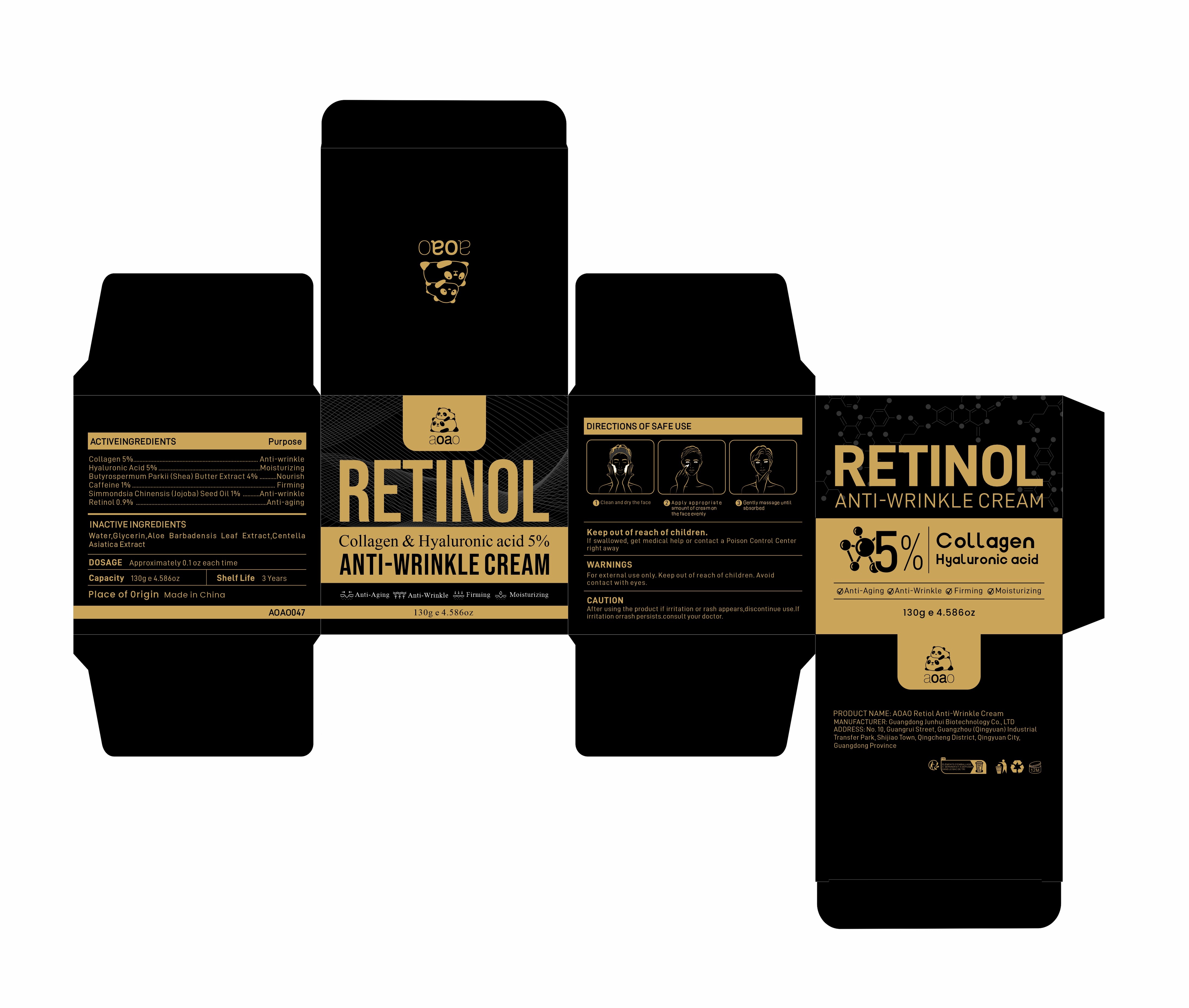 DRUG LABEL: AOAO Retiol Anti-Wrinkle Cream
NDC: 84509-026 | Form: CREAM
Manufacturer: Guangdong Junhui Biotechnology Co., LTD
Category: otc | Type: HUMAN OTC DRUG LABEL
Date: 20241020

ACTIVE INGREDIENTS: CAFFEINE 1300 mg/130 g; COLLAGEN, SOLUBLE, FISH SKIN 6500 mg/130 g; HYALURONIC ACID 6500 mg/130 g; RETINOL 1170 mg/130 g; SHEA BUTTER 5200 mg/130 g; JOJOBA OIL 1300 mg/130 g
INACTIVE INGREDIENTS: WATER; GLYCERIN; CENTELLA ASIATICA TRITERPENOIDS; ALOE VERA LEAF

Active Ingredients

Collagen 5%
Butyrospermum Parkii (Shea) Butter Extract 4%
Hyaluronic Acid 5%
Caffeine 1%
Simmondsia Chinensis (Jojoba) Seed Oil 1%
Retinol 0.9%

Purpose

Anti-wrinkle
Nourish
Moisturizing
Firming
Anti-aging

Uses

1、Clean and dry the face
2、Apply an appropriateamount of face cream evenly on the face
3、Gently massage until absorbed

Warnings

For external use only. Keep out ofreach of children.Avoid contact with eyes

Product Name

AOAO Retiol Anti-Wrinkle Cream

Keep out of reach of children

If swallowed, get medical help or contact a Poison Control Center right away

CAUTION

After using the product if irritation or rash appears,discontinue use.If irritation or
rash persists.consult your doctor.

Inactive Ingredients

Water,Glycerin，Aloe Barbadensis Leaf Extract，Centella Asiatica Extract.

DOSAGE

Approximately 0.1 oz each time

MANUFACTURER

Guangdong Junhui Biotechnology Co., LTD

Capacity

130g e 4.586 oz

ADDRESS

No. 10, Guangrui Street, Guangzhou (Qingyuan) Industrial Transfer Park, Shijiao Town, Qingcheng District, Qingyuan City, Guangdong Province

Shelf Life

3 Years

Place of Origin

Made in China